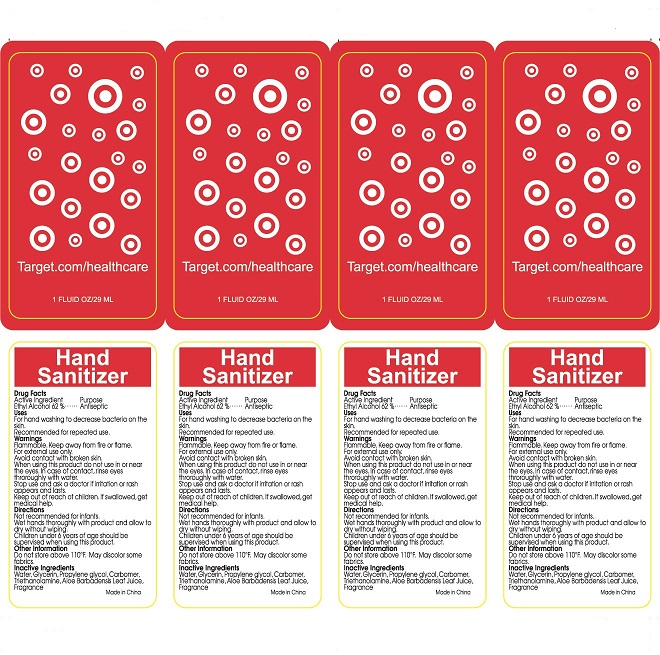 DRUG LABEL: Hand Sanitizer
NDC: 69831-0001 | Form: GEL
Manufacturer: Laser Graphics Inc.
Category: otc | Type: HUMAN OTC DRUG LABEL
Date: 20150515

ACTIVE INGREDIENTS: ALCOHOL 62 mL/100 mL
INACTIVE INGREDIENTS: WATER; ALOE VERA LEAF; GLYCERIN; PROPYLENE GLYCOL; CARBOMER INTERPOLYMER TYPE A (55000 CPS); TROLAMINE

Active Ingredient:
Ethyl Alcohol 62%

Purpose:
Antiseptic

Warnings:
Flammable. Keep away from fire or flame. For external use only. Avoid contact with broken skin.

Stop use and ask a doctor if irritation or rash appears and lasts

Keep out of reach of children. If swallowed, get medical help.

Directions:
Not recommended for infants. Wet hands thoroughly with product and allow to dry without wiping. Children under 6 years of age should be supervised when using this product.

INACTIVE INGREDIENT

Water, Glycerin,Propylene Glycol, Carbomer, Triethanolamine, Aloe barbadenis Leaf Juice, Fragrance

Other Information:
Do not store above 110 F. May discolor some fabrics.

INDICATIONS AND USAGE

For hand washing to decrease bacteria on the skin. Recommended for repeated use.

When using this product, do not use in or near eyes. In case of contact, rinse eyes thoroughly with water.